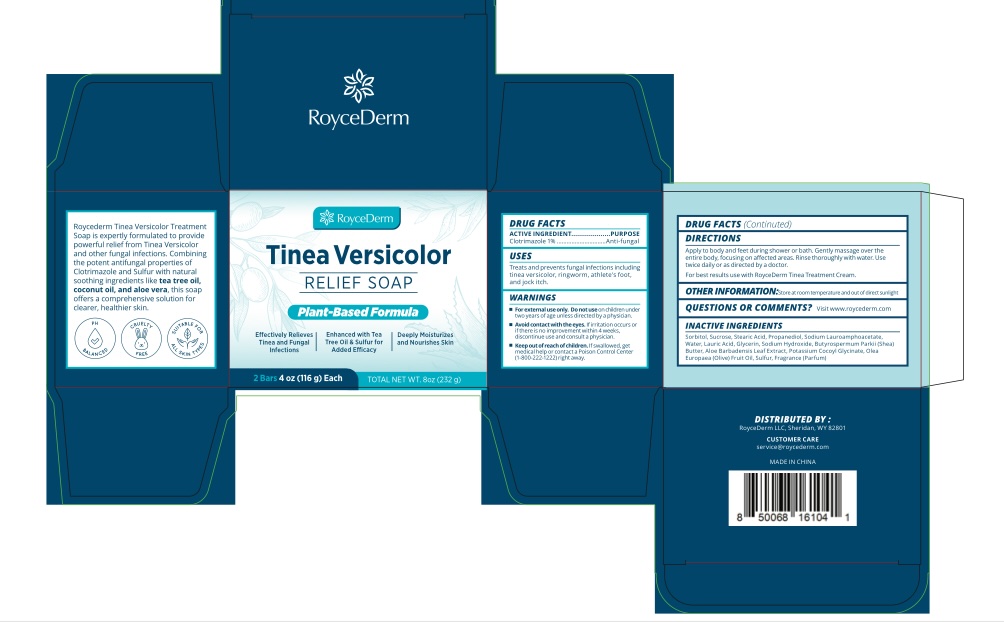 DRUG LABEL: Roycederm Tinea Versicolor Relief Soap.
NDC: 85261-311 | Form: SOAP
Manufacturer: Haikou Pucao Trading Co.,Ltd
Category: otc | Type: HUMAN OTC DRUG LABEL
Date: 20250307

ACTIVE INGREDIENTS: CLOTRIMAZOLE 1 g/100 g
INACTIVE INGREDIENTS: OLEA EUROPAEA (OLIVE) FRUIT OIL; GLYCERIN; FRAGRANCE 13576; SODIUM LAUROAMPHOACETATE; SUCROSE; WATER; ALOE BARBADENSIS LEAF; POTASSIUM COCOYL GLYCINATE; SORBITOL; BUTYROSPERMUM PARKII (SHEA) BUTTER; LAURIC ACID; SULFUR; PROPANEDIOL; SODIUM HYDROXIDE

ACTIVE INGREDIENT

Coltrimazole 1%

PURPOSE

Anti-fungal

INDICATIONS AND USAGE

Treats and prevents fungal infections including tinea versicolor, ringworm, athlete's foot, and jock itch.

DO NOT USE

For external use only. Do not use on children under two years of age unless directed by a physician.

STOP USE

Avoid contact with the eyes. If irritation occurs or if there is no improvement within 4 weeks, discontinue use and consult a physician.

Keep out of reach of children. If swallowed, get medical help or contact a Poison Control Center (1-800-222-1222) right away.

DOSAGE AND ADMINISTRATION

Apply to body and feet during shower or bath. Gently message over the entire body, focusing on affected areas. Rinse thoroughly with water. Use twice daily or as directed by a doctor.
For best results use with RoyceDerm Tinea Treatment Cream.

OTHER SAFETY INFORMATION

Store at room temperature and out of direct sunlight.

QUESTIONS

Visit www.roycederm.com

INACTIVE INGREDIENT

Sorbitol, Sucrose, Stearic Acid, Propanediol, Sodium Lauroamphoacetate, Water, Lauric Acid, Glycerin, Sodium Hydroxide, Butyrospermum Parkii (Shea) Butter, Aloe Barbadensis Leaf Extract, Potassium Cocoyl Glycinate, Olea Europaea (Olive) Fruit Oil, Sulfur, Fragrance.